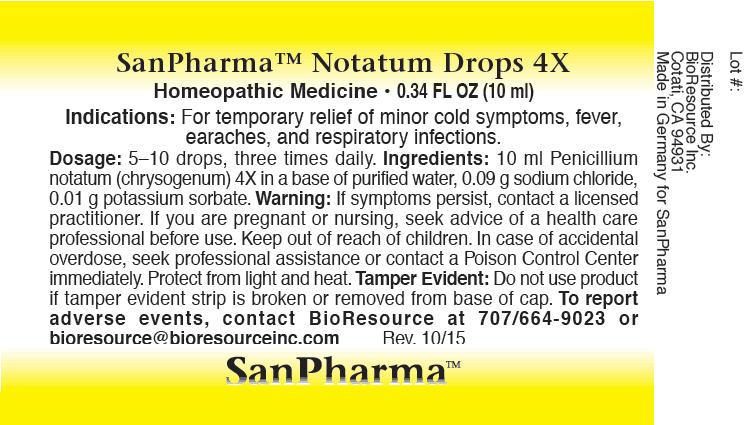 DRUG LABEL: Notatum
NDC: 54256-040 | Form: LIQUID
Manufacturer: BioResource Inc.
Category: homeopathic | Type: HUMAN OTC DRUG LABEL
Date: 20160125

ACTIVE INGREDIENTS: Penicillium Chrysogenum Var. Chrysogenum 4 [hp_X]/10 mL
INACTIVE INGREDIENTS: Water; Sodium chloride; Potassium sorbate

Notatum

PURPOSE

Indications

For temporary relief of minor cold symptoms, fever, earaches, and respiratory infections.

Dosage

5–10 drops, three times daily.

ACTIVE INGREDIENT

Ingredients

10 ml Penicillium notatum (chrysogenum) 4X in a base of purified water, 0.09 g sodium chloride, 0.01 g potassium sorbate.

Warning

If symptoms persist, contact a licensed practitioner.

PREGNANCY OR BREAST FEEDING

If you are pregnant or nursing, seek advice of a health care professional before use.

Keep out of reach of children. In case of accidental overdose, seek professional assistance or contact a Poison Control Center immediately. Protect from light and heat.

Tamper Evident

Do not use product if tamper evident strip is broken or removed from base of cap. To report adverse events, contact BioResource at 707/664-9023 or bioresource@bioresourceinc.com

Distributed By:
BioResource Inc.
Cotati, CA 94931

PRINCIPAL DISPLAY PANEL - 10 ml Bottle Label

SanPharma™ Notatum Drops 4X

Homeopathic Medicine • 0.34 FL OZ (10 ml)

SanPharma™